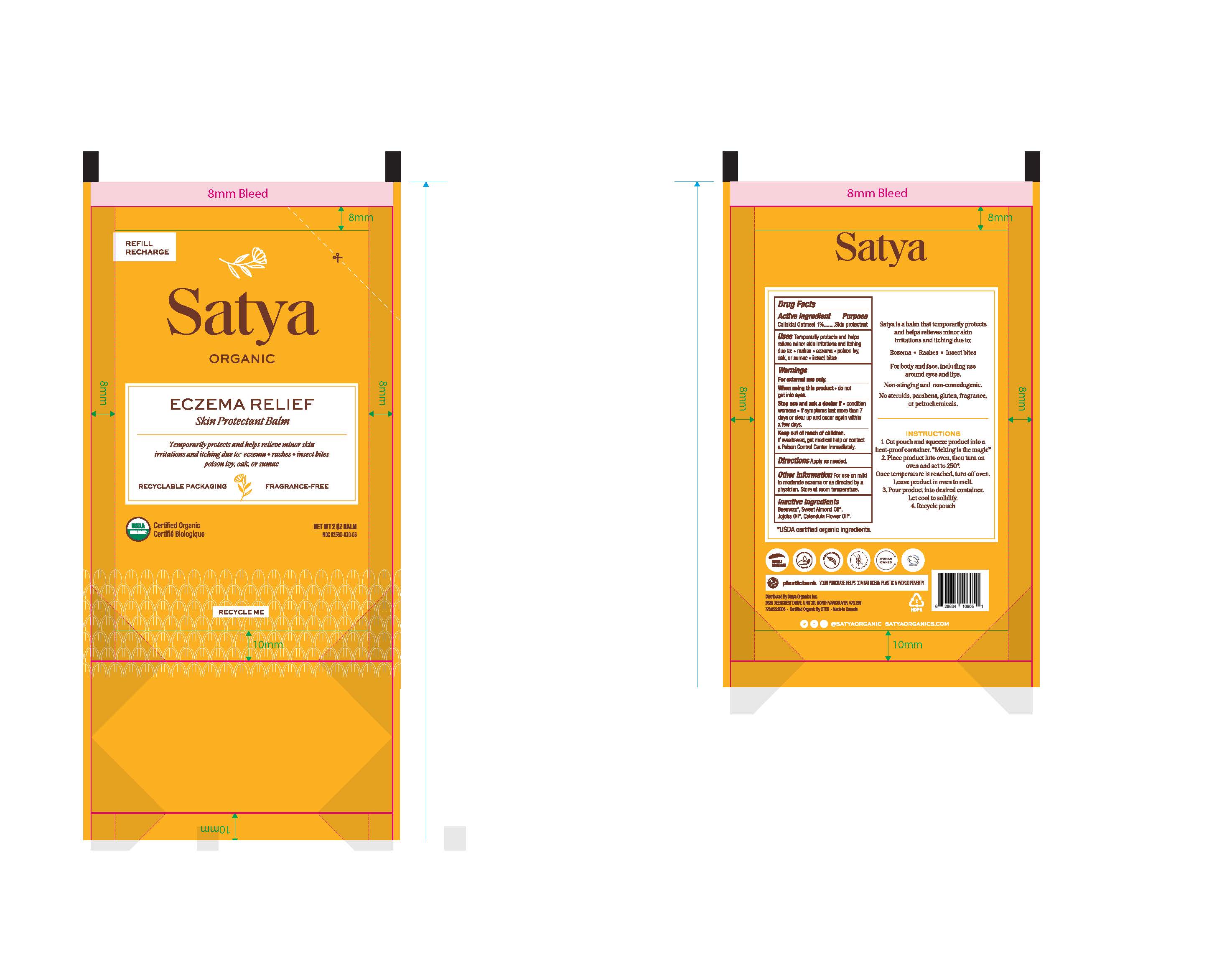 DRUG LABEL: Satya ORGANIC FRAGRANCE-FREE ECZEMA RELIEF
NDC: 82590-030 | Form: OINTMENT
Manufacturer: Satya Organic Inc.
Category: otc | Type: HUMAN OTC DRUG LABEL
Date: 20240131

ACTIVE INGREDIENTS: OATMEAL 10 mg/1 mL
INACTIVE INGREDIENTS: SYNTHETIC BEESWAX; CALENDULA OFFICINALIS FLOWER; JOJOBA OIL; ALMOND OIL

Satya ORGANIC FRAGRANCE-FREE ECZEMA RELIEF

Active IngredientColloidal oatmeal 1%

PURPOSE

PurposesSkin protectant

INDICATIONS AND USAGE

Uses temporarily protects and helps relieve minor skin irritation and itching due to:

• rashes • eczema • poison ivy, oak or sumac • insect bites

Warnings For external use only.

When using this product do not get into eyes

Stop use and ask a doctor if

- condition worsens
- symptoms last more than 7 days or clear up and occur again within a few days

Keep out of reach of children. If swallowed, get medical help or contact a Poison Control Center right away.

Directions

apply as needed

INACTIVE INGREDIENT

InactiveingredientsBeeswax*, Calendula Flower Oil*, Jojoba Oil*, Sweet Almond Oil.*

* USDA certified organic ingredient.

Questions? 778.655.9006

@SATYAORGANIC

PACKAGE LABEL

Refill

Satya

ORGANIC

ECZEMA RELIEF

Skin Protectant Balm

Temporarily protects and helps relieve minor skin irritations and itching due to:

eczema ♦ rashes ♦ insect bites ♦ poison ivy, oat or sumac

Recycalble Packaging Fragrance-Free

USDA Certified Organic

NET WT 2 OZ BALM

NDC 82590-030-03